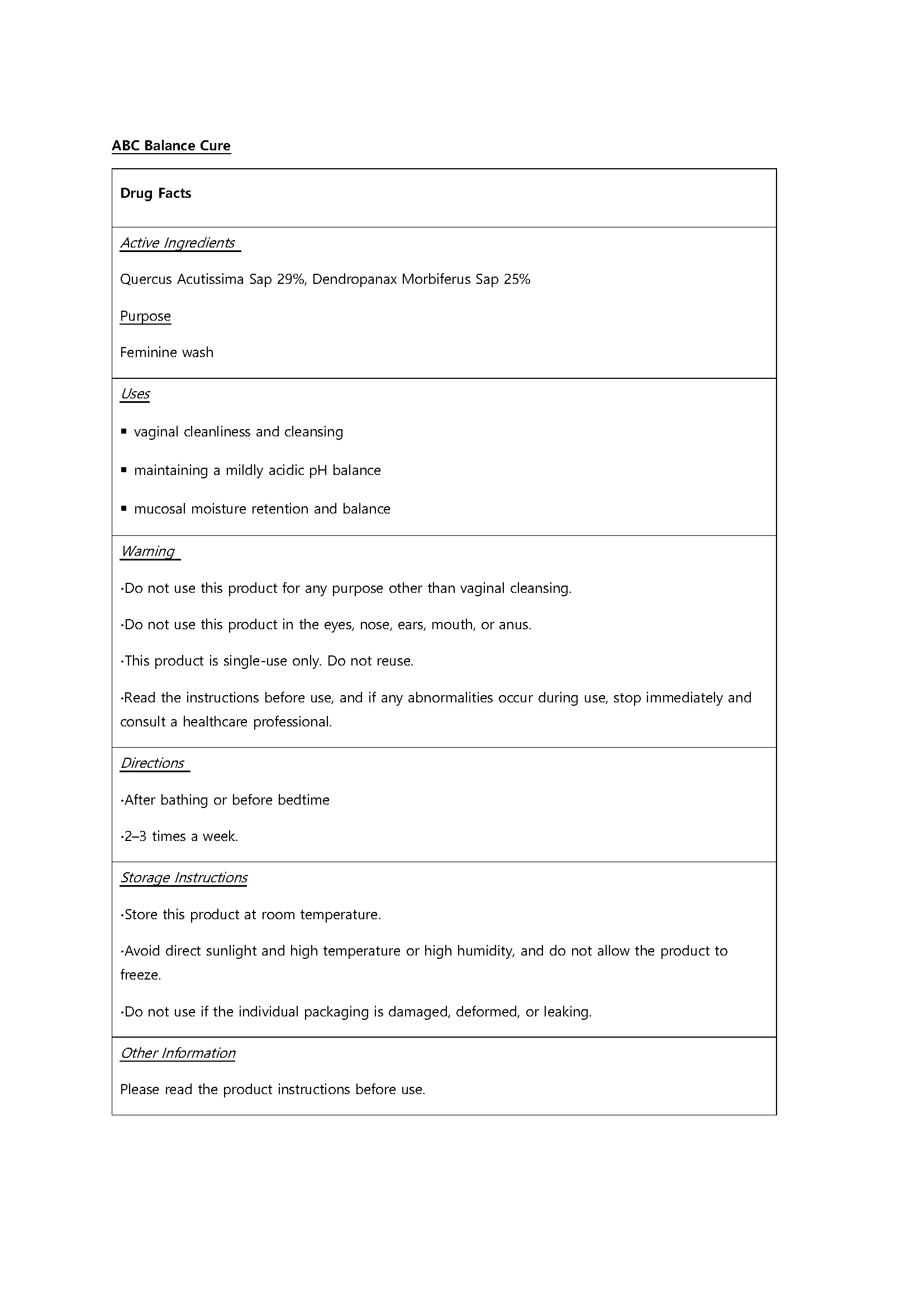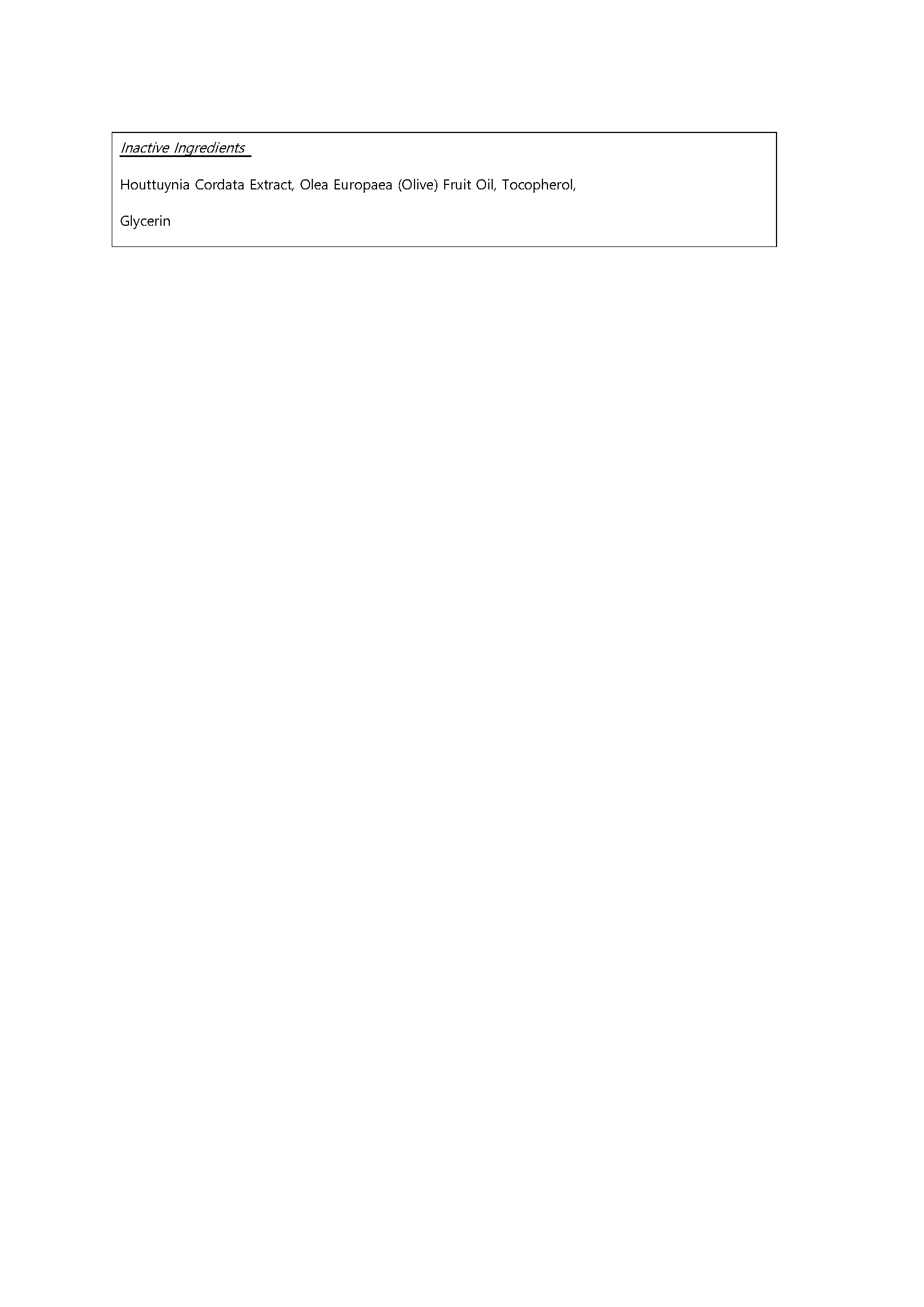 DRUG LABEL: ABC Balance Cure
NDC: 87368-0001 | Form: LIQUID
Manufacturer: ABCPharm co.,LTD
Category: otc | Type: HUMAN OTC DRUG LABEL
Date: 20260202

ACTIVE INGREDIENTS: QUERCUS ACUTISSIMA WHOLE 29 g/100 mL
INACTIVE INGREDIENTS: GLYCERIN

Drug Facts

ACTIVE INGREDIENT

Quercus Acutissima Sap 29%, Dendropanax Morbiferus Sap 25%

INACTIVE INGREDIENT

Houttuynia Cordata Extract, Olea Europaea (Olive) Fruit Oil, Tocopherol,

Glycerin

PURPOSE

Feminine wash

keep out of reach of the children

∙Do not use this product for any purpose other than vaginal cleansing.

∙Do not use this product in the eyes, nose, ears, mouth, or anus.

∙This product is single-use only. Do not reuse.

∙Read the instructions before use, and if any abnormalities occur during use, stop immediately and consult a healthcare professional.

INDICATIONS AND USAGE

∙After bathing or before bedtime

∙2–3 times a week.

DOSAGE AND ADMINISTRATION

for external use only